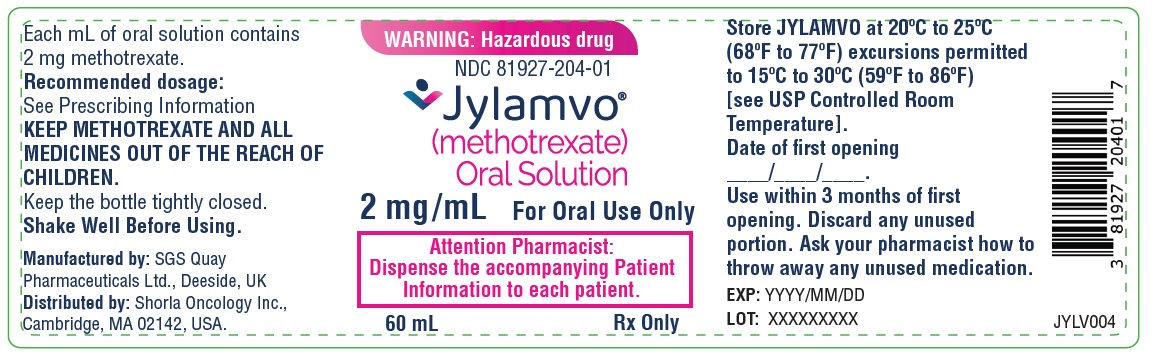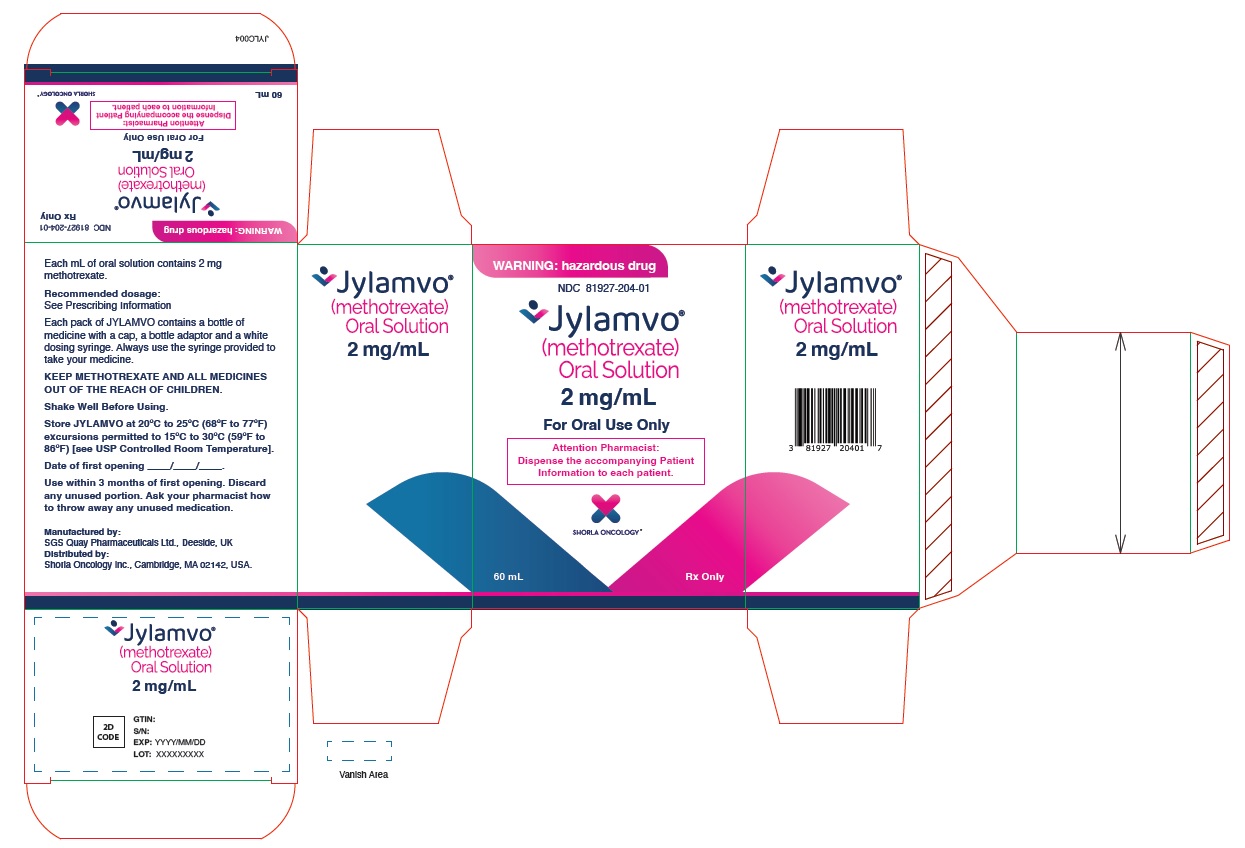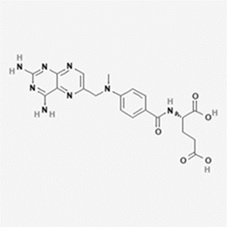 DRUG LABEL: JYLAMVO
NDC: 81927-204 | Form: SOLUTION
Manufacturer: SHORLA ONCOLOGY INC.
Category: prescription | Type: HUMAN PRESCRIPTION DRUG LABEL
Date: 20251215

ACTIVE INGREDIENTS: METHOTREXATE 2 mg/1 mL
INACTIVE INGREDIENTS: POLYETHYLENE GLYCOL; GLYCERIN; SUCRALOSE; ETHYLPARABEN; METHYLPARABEN SODIUM; CITRIC ACID MONOHYDRATE; SODIUM CITRATE; WATER

HIGHLIGHTS OF PRESCRIBING INFORMATION

These highlights do not include all the information needed to use JYLAMVO® safely and effectively. See full prescribing information for JYLAMVO®.
JYLAMVO®(methotrexate) oral solution
Initial U.S. Approval: 1953

WARNING: EMBRYO-FETAL TOXICITY, HYPERSENSITIVITY REACTIONS AND SEVERE ADVERSE REACTIONS

See full prescribing information for complete boxed warning.

- Methotrexate can cause embryo-fetal toxicity, including fetal death. For non-neoplastic diseases, Jylamvo is contraindicated in pregnancy. For neoplastic diseases, advise patients of reproductive potential of the potential risk to a fetus and to use effective contraception during and after treatment with Jylamvo (4, 5.1, 8.1, 8.3).
- Jylamvo is contraindicated in patients with a history of severe hypersensitivity reactions to methotrexate, including anaphylaxis (4, 5.2).
- Serious adverse reactions, including death, have been reported with methotrexate. Closely monitor for infections and adverse reactions of the bone marrow, gastrointestinal tract, liver, lungs, skin, and kidneys. Withhold or discontinue Jylamvo as appropriate (5.3, 5.4, 5.5, 5.6, 5.7, 5.8, 5.11).

RECENT MAJOR CHANGES

Indications and Usage (1.1 and 1.3) 10/2024
Dosage and Administration (2.4) 10/2024

1 INDICATIONS AND USAGE

JYLAMVO is a folate analog metabolic inhibitor indicated for the:

- Treatment of adults and pediatric patients with acute lymphoblastic leukemia (ALL) as part of a combination chemotherapy maintenance regimen (1.1)
- Treatment of adults with mycosis fungoides (1.1)
- Treatment of adults with relapsed or refractory non-Hodgkin lymphoma as part of a metronomic combination regimen (1.1)
- Treatment of adults with rheumatoid arthritis (1.2)
- Treatment of pediatric patients with polyarticular juvenile idiopathic arthritis (pJIA) (1.3)
- Treatment of adults with severe psoriasis (1.4)

2 DOSAGE AND ADMINISTRATION

- Verify pregnancy status in females of reproductive potential before starting JYLAMVO. (2.1, 4, 5.1)
- Instruct patients and caregivers to take the recommended dosage as directed, because medication errors have led to deaths. (2.1, 5.9)
- ALL: The recommended dosage is 20 mg/m^2 orally once weekly as a part of a combination chemotherapy maintenance regimen. (2.2)
- Mycosis fungoides: The recommended dosage is 25 mg to 75 mg orally once weekly as monotherapy; 10 mg/m^2 orally twice weekly as part of combination chemotherapy. (2.2)
- Relapsed or refractory non-Hodgkin lymphoma: The recommended dosage is 2.5 mg orally two to four times per week as part of metronomic combination chemotherapy. (2.2)
- Rheumatoid Arthritis: The recommended starting dosage is 7.5 mg orally once weekly; adjust dose to achieve an optimal response. (2.3)
- pJIA: The recommended starting dosage is 10 mg/m^2 orally once weekly; adjust dose to achieve an optimal response. (2.4)
- Psoriasis: The recommended dosage is 10 mg to 25 mg orally once weekly until adequate response is achieved. (2.5)

3 DOSAGE FORMS AND STRENGTHS

Oral solution: 2 mg/mL (3)

4 CONTRAINDICATIONS

- Pregnant patients with non-neoplastic diseases (4)
- History of severe hypersensitivity to methotrexate (4)

5 WARNINGS AND PRECAUTIONS

- Serious Infections: Monitor patients for infection during and after treatment with JYLAMVO. Withhold or discontinue methotrexate for serious infections as appropriate. (5.11)
- Neurotoxicity: Monitor patients for neurotoxicity and withhold or discontinue methotrexate as appropriate. (5.12)
- Secondary Malignancies: Can occur with methotrexate. (5.13)
- Tumor Lysis Syndrome: Institute appropriate prophylactic measures in patients at risk for tumor lysis syndrome prior to initiation of JYLAMVO. (5.14)
- Immunizations and Risks Associated with Live Vaccines: Immunizations with live vaccines is not recommended. Follow current vaccination practice guidelines. (5.15)
- Infertility: Can cause impairment of fertility, oligospermia, and menstrual dysfunction. (5.16, 8.3)

6 ADVERSE REACTIONS

Common adverse reactions include ulcerative stomatitis, leukopenia, nausea, abdominal distress. (6.1)

To report SUSPECTED ADVERSE REACTIONS, contact Shorla Oncology at 844-9-SHORLA or FDA at 1-800-FDA-1088 or www.fda.gov/medwatch.

7 DRUG INTERACTIONS

Refer to the full prescribing information for drug interactions with JYLAMVO. (7)

8 USE IN SPECIFIC POPULATIONS

Lactation: Advise women not to breastfeed. (8.2)

FULL PRESCRIBING INFORMATION

WARNING: EMBRYO-FETAL TOXICITY, HYPERSENSITIVITY REACTIONS AND SEVERE ADVERSE REACTIONS

- Methotrexate can cause embryo-fetal toxicity, including fetal death. For non-neoplastic diseases, Jylamvo is contraindicated in pregnancy. For neoplastic diseases, advise females and males of reproductive potential to use effective contraception during and after treatment with Jylamvo [see Contraindications (4), Warnings and Precautions (5.1), Use in Specific Populations (8.1, 8.3)].
- Jylamvo is contraindicated in patients with a history of severe hypersensitivity reactions to methotrexate, including anaphylaxis [Contraindications (4), Warnings and Precautions (5.2)].
- Serious adverse reactions, including death, have been reported with methotrexate. Closely monitor for infections and adverse reactions of the bone marrow, gastrointestinal tract, liver, lungs, skin, and kidneys. Withhold or discontinue Jylamvo as appropriate [Warnings and Precautions (5.3, 5.4, 5.5, 5.6, 5.7, 5.8, 5.11)].

1 INDICATIONS AND USAGE

1.1 Neoplastic Diseases

JYLAMVO is indicated for the:

- treatment of adults and pediatric patients with acute lymphoblastic leukemia (ALL) as part of a combination chemotherapy maintenance regimen.
- treatment of adults with mycosis fungoides (cutaneous T-cell lymphoma) as a single agent or as part of a combination chemotherapy regimen.
- treatment of adults with relapsed or refractory non-Hodgkin lymphomas as part of a metronomic combination chemotherapy regimen.

1.2 Rheumatoid Arthritis

JYLAMVO is indicated for the treatment of adults with rheumatoid arthritis.

1.3 Polyarticular Juvenile Idiopathic Arthritis

JYLAMVO is indicated for the treatment of pediatric patients with polyarticular Juvenile Idiopathic Arthritis (pJIA).

1.4 Psoriasis

JYLAMVO is indicated for the treatment of adults with severe psoriasis.

2 DOSAGE AND ADMINISTRATION

2.1 Important Dosage and Safety Information

Verify pregnancy status in females of reproductive potential before starting JYLAMVO [see Contraindications (4), Warnings and Precautions (5.1)].

Instruct patients and caregivers on how to measure and administer the recommended dosage using the copackaged syringe and bottle adaptor as directed, because medication errors have led to deaths [see Warnings and Precautions (5.9)].

Ensure patients and caregivers understand the instructions provided in the Patient Information on proper dosing of JYLAMVO based on volume (mL) utilizing the copackaged syringe before use.

Advise patients and caregivers to only use the copackaged syringe to measure JYLAMVO and that a teaspoon is not an appropriate measuring device. The dosing syringe utilizes mL as the unit of measure; ensure that the correct dose expressed in volume (mL) is prescribed. JYLAMVO contains 2 mg of methotrexate in each mL of solution.

JYLAMVO is intended for oral use only. When switching the patient’s dosing regimen from a methotrexate product for oral administration to a methotrexate product for intravenous, intramuscular, or subcutaneous administration, an alternative dosing regimen may be necessary due to potential differences in bioavailability.

JYLAMVO is a hazardous drug. Follow applicable special handling and disposal procedures^1.

2.2 Recommended Dosage for Neoplastic Diseases

Acute Lymphoblastic Leukemia

The recommended starting dosage of JYLAMVO is 20 mg/m^2 orally once weekly, as part of a combination chemotherapy maintenance regimen. After initiating JYLAMVO, periodically monitor absolute neutrophil count (ANC) and platelet count and adjust the dose to maintain ANC at a desirable level and for excessive myelosuppression.

Mycosis Fungoides

The recommended dosage of JYLAMVO is 25 mg to 75 mg orally once weekly when administered as a single agent or 10 mg/m^2 orally twice weekly as part of a combination chemotherapy regimen.

Relapsed or Refractory Non-Hodgkin Lymphomas

The recommended dosage of JYLAMVO is 2.5 mg orally 2 to 4 times per week (maximum 10 mg per week) as part of a metronomic combination chemotherapy regimen.

2.3 Recommended Dosage for Rheumatoid Arthritis

The recommended starting dosage of JYLAMVO is 7.5 mg orally once weekly with escalation to achieve optimal response. Dosages of more than 20 mg once weekly result in an increased risk of serious adverse reactions, including myelosuppression. When responses are observed, the majority occur between 3 and 6 weeks from initiation of treatment; however, responses have occurred up to 12 weeks after treatment initiation.

Administer folic acid or folinic acid to reduce the risk of methotrexate adverse reactions [see Warnings and Precautions (5.10)].

2.4 Recommended Dosage for Polyarticular Juvenile Idiopathic Arthritis

The recommended starting dose of JYLAMVO is 10 mg/m^2 orally once weekly with escalation to achieve optimal response. Dosages of more than 30 mg/m^2 once weekly result in an increased risk of serious adverse reactions, including myelosuppression. When responses are observed, the majority occurred between 3 and 6 weeks from initiation of treatment; however, responses have occurred up to 12 weeks after treatment initiation.

Administer folic acid or folinic acid to reduce the risk of methotrexate adverse reactions [see Warnings and Precautions (5.10)].

2.5 Recommended Dosage for Psoriasis

The recommended dosage of JYLAMVO is 10 mg to 25 mg orally once weekly until an adequate response is achieved. Adjust the dose gradually to achieve optimal clinical response; do not exceed a dose of 30 mg per week. Once optimal clinical response has been achieved, reduce the dosage to the lowest possible dosing regimen.

Administer folic acid or folinic acid supplementation to reduce the risk of methotrexate adverse reactions [see Warnings and Precautions (5.10)].

2.6 Dosage Modifications for Adverse Reactions

Discontinue JYLAMVO for:

- Anaphylaxis or other severe hypersensitivity reactions [see Warnings and Precautions (5.2)]
- Lymphoproliferative disease [see Warnings and Precautions (5.13)]

Withhold, dose reduce or discontinue JYLAMVO as appropriate for:

- Myelosuppression [see Warnings and Precautions (5.3)]

Withhold or discontinue JYLAMVO as appropriate for:

- Severe gastrointestinal toxicity [see Warnings and Precautions (5.4)]
- Hepatotoxicity [see Warnings and Precautions (5.5)]
- Pulmonary toxicity [see Warnings and Precautions (5.6)]
- Severe dermatologic reactions [see Warnings and Precautions (5.7)]
- Severe renal toxicity [see Warnings and Precautions (5.8)]
- Serious infections [see Warnings and Precautions (5.11)]
- Neurotoxicity [see Warnings and Precautions (5.12)]

3 DOSAGE FORMS AND STRENGTHS

Oral solution: clear yellow solution containing methotrexate 2 mg/mL.

4 CONTRAINDICATIONS

JYLAMVO is contraindicated in:

- Pregnant women for treatment of non-neoplastic diseases [see Warnings and Precautions (5.1), and Use in Specific Populations (8.1, 8.3)].
- Patients with a history of a severe hypersensitivity reactions, including anaphylaxis, to methotrexate [see Warnings and Precautions (5.2)].

5 WARNINGS AND PRECAUTIONS

5.1 Embryo-Fetal Toxicity

Based on published reports and its mechanism of action, methotrexate can cause fetal harm, including fetal death, when administered to a pregnant woman. JYLAMVO is contraindicated for use in pregnant women receiving JYLAMVO for the treatment of non-malignant diseases. Advise pregnant women with neoplastic diseases of the potential risk to a fetus. Advise females of reproductive potential to use effective contraception during treatment with JYLAMVO and for 6 months after the final dose. Advise males with female partners of reproductive potential to use effective contraception during JYLAMVO treatment and for at least 3 months after the final dose [see Contraindications (4), Use in Specific Populations (8.1, 8.3)].

5.2 Hypersensitivity Reactions

Hypersensitivity reactions, including anaphylaxis, can occur with methotrexate [see Contraindications (4), Adverse Reactions (6.1)].

If anaphylaxis or other serious hypersensitivity reaction occurs, immediately and permanently discontinue JYLAMVO [see Dosage and Administration (2.6)].

5.3 Myelosuppression

Methotrexate suppresses hematopoiesis and can cause severe and life-threatening pancytopenia, anemia, leukopenia, neutropenia, and thrombocytopenia [see Adverse Reactions (6.1)].

Obtain blood counts at baseline, periodically during treatment, and as clinically indicated. Monitor patients for clinical complications of myelosuppression. Withhold, dose reduce, or discontinue JYLAMVO taking into account the importance of JYLAMVO treatment in the context of the severity of the disease being treated, the severity of the adverse drug reaction, and availability of alternative therapy [see Dosage and Administration (2.6)].

5.4 Gastrointestinal Toxicity

Diarrhea, vomiting, nausea, and stomatitis occurred in up to 10% of patients receiving methotrexate for treatment of non-neoplastic diseases. Hemorrhagic enteritis and fatal intestinal perforation have been reported [see Adverse Reactions (6.1, 6.2)]. Patients with peptic ulcer disease or ulcerative colitis are at a greater risk of developing severe gastrointestinal adverse reactions [see Drug Interactions (7.1)].

Withhold or discontinue JYLAMVO for severe gastrointestinal toxicity taking into account the importance of JYLAMVO treatment in the context of the severity of the disease being treated, the severity of the adverse drug reaction, and availability of alternative therapy [see Dosage and Administration (2.6)].

5.5 Hepatotoxicity

Methotrexate can cause severe and potentially irreversible hepatotoxicity, including fibrosis, cirrhosis, and fatal liver failure [see Adverse Reactions (6.1)]. The safety of JYLAMVO in patients with hepatic disease is unknown.

The risk of hepatotoxicity is increased with heavy alcohol consumption. In patients with psoriasis, fibrosis or cirrhosis may occur in the absence of symptoms or abnormal liver tests; the risk of hepatotoxicity appears to increase with total cumulative dose and generally occurs after receipt of a total cumulative dose of 1.5 g or more.

Monitor liver tests at baseline, periodically during treatment and as clinically indicated. Withhold or discontinue JYLAMVO taking into account the importance of JYLAMVO treatment in the context of the severity of the disease being treated, the severity of the adverse drug reaction, and availability of alternative therapy [see Dosage and Administration (2.6)].

5.6 Pulmonary Toxicity

Pulmonary toxicity, including acute or chronic interstitial pneumonitis and irreversible or fatal cases, can occur with methotrexate [see Adverse Reactions (6.1, 6.2)].

Monitor patients for pulmonary toxicity and withhold or discontinue JYLAMVO taking into account the importance of JYLAMVO treatment in the context of the severity of the disease being treated, the severity of the adverse drug reaction, and availability of alternative therapy [see Dosage and Administration (2.6)].

5.7 Dermatologic Reactions

Severe, including fatal dermatologic reactions, such as toxic epidermal necrolysis, Stevens-Johnson syndrome, exfoliative dermatitis, skin necrosis, and erythema multiforme, can occur with methotrexate [see Adverse Reactions (6.1, 6.2)].

Exposure to ultraviolet radiation while taking methotrexate may aggravate psoriasis.

Methotrexate can cause radiation recall dermatitis and photodermatitis (sunburn) reactivation.

Monitor patients for dermatologic toxicity and withhold or permanently discontinue JYLAMVO for severe dermatologic reactions taking into account the importance of JYLAMVO treatment in the context of the severity of the disease being treated, the severity of the adverse drug reaction, and availability of alternative therapy [see Dosage and Administration (2.6)]. Advise patients to avoid excessive sun exposure and use sun protection measures.

5.8 Renal Toxicity

Methotrexate can cause renal toxicity, including irreversible acute renal failure [see Adverse Reactions (6.2)].

Monitor renal function at baseline, periodically during treatment and as clinically indicated. Withhold or discontinue JYLAMVO for severe renal toxicity taking into account the importance of JYLAMVO treatment in the context of the severity of the disease being treated, the severity of the adverse drug reaction, and availability of alternative therapy [see Dosage and Administration (2.6)].

Administer glucarpidase in patients with toxic plasma methotrexate concentrations (> 1 micromole per liter) and delayed methotrexate clearance due to impaired renal function. Refer to the glucarpidase prescribing information for additional information.

5.9 Risk of Serious Adverse Reactions with Medication Error

Deaths occurred in patients as a result of medication errors. Most commonly, these errors occurred in patients who were taking methotrexate daily when a weekly dosing regimen was prescribed.

For patients prescribed a once weekly dosing regimen, instruct patients and caregivers to take the recommended dosage as directed, because medication errors have led to death.

Instruct patients and caregivers on how to measure, dose, and administer the recommended dosage as directed [see Dosage and Administration (2)].

5.10 Folic Acid Supplementation

Neoplastic Diseases

Products containing folic acid or its derivatives may decrease the clinical effectiveness of methotrexate. Therefore, instruct patients not to take products containing folic acid or folinic acid unless directed to do so by their healthcare provider.

Non-neoplastic Diseases

Folate deficiency may increase methotrexate adverse reactions. Administer folic acid or folinic acid for patients with rheumatoid arthritis, pJIA, and psoriasis [see Dosage and Administration (2.3, 2.4, 2.5)].

5.11 Serious Infections

Patients treated with methotrexate are at increased risk for developing life-threatening or fatal bacterial, fungal, or viral infections, including opportunistic infections such as Pneumocystis jiroveci pneumonia, invasive fungal infections, hepatitis B reactivation, tuberculosis primary infection or reactivation, and disseminated Herpes zoster and cytomegalovirus infections [see Adverse Reactions (6.2)].

Monitor patients for infection during and after treatment with JYLAMVO. Withhold or discontinue JYLAMVO for serious infections taking into account the importance of JYLAMVO treatment in the context of the severity of the disease being treated, the severity of the adverse drug reaction, and availability of alternative therapy [see Dosage and Administration (2.6)].

5.12 Neurotoxicity

Methotrexate can cause severe acute and chronic neurotoxicity, which can be progressive, irreversible, and fatal [see Adverse Reactions (6.2)]. The risk of leukoencephalopathy is increased in patients who received prior cranial radiation.

Monitor patients for neurotoxicity and withhold or discontinue JYLAMVO taking into account the importance of JYLAMVO treatment in the context of the severity of the disease being treated, the severity of the adverse drug reaction, and availability of alternative therapy [see Dosage and Administration (2.6)].

5.13 Secondary Malignancies

Secondary malignancies can occur with methotrexate [see Adverse Reactions (6.2)]. The risk of cutaneous malignancies is further increased when cyclosporine is administered to patients with psoriasis who received prior methotrexate.

In some cases, lymphoproliferative disease occurring during therapy with low-dose methotrexate regressed completely following withdrawal of methotrexate. If lymphoproliferative disease occurs, discontinue JYLAMVO [see Dosage and Administration (2.6)].

5.14 Tumor Lysis Syndrome

Methotrexate can induce tumor lysis syndrome in patients with rapidly growing tumors. Institute appropriate prophylactic measures in patients at risk for tumor lysis syndrome prior to initiation of JYLAMVO.

5.15 Immunization and Risks Associated with Live Vaccines

Disseminated infections following administration of live vaccines have been reported. Immunization with live vaccines is not recommended during treatment. Follow current vaccination practice guidelines for administration of immunizations in patients receiving JYLAMVO.

Update immunizations according to immunization guidelines prior to initiating JYLAMVO. The interval between live vaccinations and initiation of methotrexate should be in accordance with current vaccination guidelines for patients on immunosuppressive agents.

5.16 Infertility

Based on published reports, methotrexate can cause impairment of fertility, oligospermia, and menstrual dysfunction. It is not known if the infertility may be reversible. Discuss the risk of infertility with females and males of reproductive potential [see Use in Specific Populations (8.3)].

5.17 Increased Risk of Adverse Reactions Due to Third-Space Accumulation

Methotrexate accumulates in third-spaces (e.g., pleural effusions or ascites), which results in prolonged elimination and increases the risk of adverse reactions. Evacuate significant third-space accumulations prior to JYLAMVO administration taking into account the importance of JYLAMVO treatment in the context of the severity of the disease being treated, the severity of the adverse drug reaction, and availability of alternative therapy.

6 ADVERSE REACTIONS

The following clinically significant adverse reactions are described elsewhere in the labeling:

- Hypersensitivity Reactions [see Warnings and Precautions (5.2)]
- Myelosuppression [see Warnings and Precautions (5.3)]
- Gastrointestinal Toxicity [see Warnings and Precautions (5.4)]
- Hepatotoxicity [see Warnings and Precautions (5.5)]
- Pulmonary Toxicity [see Warnings and Precautions (5.6)]
- Dermatologic Reactions [see Warnings and Precautions (5.7)]
- Renal Toxicity [see Warnings and Precautions (5.8)]
- Serious Infections [see Warnings and Precautions (5.11)]
- Neurotoxicity [see Warnings and Precautions (5.12)]
- Secondary Malignancies [see Warnings and Precautions (5.13)]
- Tumor Lysis Syndrome [see Warnings and Precautions (5.14)]
- Increased Risk of Adverse Reactions Due to Third-Space Accumulation [see Warnings and Precautions (5.17)]

6.1 Clinical Trials Experience

Because clinical trials are conducted under widely varying conditions, adverse reaction rates observed in the clinical trials of a drug cannot be directly compared to rates in the clinical trials of another drug and may not reflect the rates observed in practice.

Common adverse reactions were: ulcerative stomatitis, leukopenia, nausea, and abdominal distress. Other clinically relevant adverse reactions were infection, malaise, fatigue, chills, fever, and dizziness.

Rheumatoid Arthritis

The most common adverse reactions of methotrexate that exceeded the rate of placebo in 12- to 18-week double-blind studies in patients (n=128) with rheumatoid arthritis are listed below. Patients received methotrexate 7.5 mg to 15 mg orally once weekly. Most patients received concomitant nonsteroidal anti-inflammatory drugs (NSAIDs) and some also received corticosteroids. Hepatic histology was not examined in these short-term studies.

Incidence ≥10%: Elevated liver tests 15%, nausea/vomiting 10%

Incidence 3% to <10%: Stomatitis, thrombocytopenia (platelet count < 100,000/mm^3)

Incidence 1% to <3%: Rash/pruritus/dermatitis, diarrhea, alopecia, leukopenia (white blood cell count < 3000/mm^3), pancytopenia, dizziness

Two other controlled trials of patients (n=680) with rheumatoid arthritis who received methotrexate 7.5 mg to 15 mg orally once weekly showed the following serious adverse reaction:

Incidence 1%: Interstitial pneumonitis

Other less common adverse reactions were: anemia, headache, upper respiratory infection, anorexia, arthralgias, chest pain, coughing, dysuria, eye discomfort, epistaxis, fever, infection, sweating, tinnitus, vaginal discharge.

Polyarticular Juvenile Idiopathic Arthritis (pJIA)

The most common adverse reactions reported in patients 2 to 18 years of age with pJIA treated with methotrexate 5 mg/m^2 to 20 mg/m^2 orally once weekly or 0.1 mg/kg to 0.65 mg/kg orally once weekly were as follows: elevated liver tests 14%; gastrointestinal reactions (e.g., nausea, vomiting, diarrhea) 11%; stomatitis 2%; leukopenia 2%; headache 1.2%; alopecia 0.5%; dizziness 0.2%; rash 0.2%. Most patients received concomitant NSAIDs and some also received corticosteroids.

Psoriasis

In two published series of adults with psoriasis (n=204, 248) who received methotrexate up to 25 mg per week for up to 4 years, adverse reaction rates were similar to those in patients with rheumatoid arthritis, except for alopecia, photosensitivity, and “burning of skin lesions” (3% to 10% each). Painful plaque erosions have been reported.

6.2 Postmarketing Experience

The following adverse reactions have been identified during postapproval use of methotrexate. Because these reactions are reported voluntarily from a population of uncertain size, it is not always possible to reliably estimate their frequency or establish a causal relationship to drug exposure.

Cardiovascular: Thromboembolic events (including arterial thrombosis, cerebral thrombosis, deep vein thrombosis, retinal vein thrombosis, thrombophlebitis, and pulmonary embolus), pericarditis, pericardial effusion, hypotension, sudden death

Endocrine: Diabetes

Eye: Optic neuropathy, blurred vision, ocular pain, conjunctivitis, xerophthalmia

Gastrointestinal: Hemorrhagic enteritis, intestinal perforation, gingivitis, pancreatitis, pharyngitis, hematemesis, melena, gastrointestinal ulceration

Hematology: Aplastic anemia, lymphadenopathy, hypogammaglobulinemia

Hepatobiliary: Acute hepatitis, decreased serum albumin, fibrosis, cirrhosis

Immune system: Anaphylaxis, anaphylactoid reactions, vasculitis

Metabolism: Hyperglycemia

Musculoskeletal: Stress fracture, soft tissue and bone necrosis, arthralgia, myalgia, osteoporosis

Nervous system: Headaches, drowsiness, blurred vision, speech impairment (including dysarthria and aphasia), transient cognitive dysfunction, mood alteration, unusual cranial sensations, paresis, encephalopathy, and convulsions.

Renal: Azotemia, hematuria, proteinuria, cystitis

Reproductive: Defective oogenesis or spermatogenesis, loss of libido, impotence, gynecomastia, menstrual dysfunction

Respiratory: Pulmonary fibrosis, respiratory failure, chronic interstitial obstructive pulmonary disease, pleuritic pain and thickening, alveolitis

Skin: Toxic epidermal necrolysis, Stevens-Johnson syndrome, exfoliative dermatitis, skin necrosis, and erythema multiforme, erythematous rashes, pruritus, alopecia, skin ulceration, accelerated nodulosis, urticaria, pigmentary changes, ecchymosis, telangiectasia, photosensitivity, acne, furunculosis

7 DRUG INTERACTIONS

7.1 Effects of Other Drugs on Methotrexate

Drugs that Increase Methotrexate Exposure

Coadministration of methotrexate with the following products may increase methotrexate plasma concentrations, which may increase the risk of methotrexate severe adverse reactions. In some cases, the coadministration of methotrexate with these products may also subsequently reduce active metabolite formation, which may decrease the clinical effectiveness of methotrexate. Increased organ specific adverse reactions may also occur when methotrexate is coadministered with hepatotoxic or nephrotoxic products.

If coadministration cannot be avoided, monitor closely for methotrexate adverse reactions when coadministered with:

- Oral antibiotics (including neomycin)
- Oral or intravenous penicillin or sulfonamide antibiotics
- Antifolate drugs (e.g., dapsone, pemetrexed, pyrimethamine and sulfonamides)
- Aspirin and other nonsteroidal anti-inflammatory drugs
- Hepatotoxic products
- Highly protein-bound drugs (e.g., oral anticoagulants, phenytoin, salicylates, sulfonamides, sulfonylureas, and tetracyclines)
- Probenecid
- Proton pump inhibitors
- Weak acids (e.g., salicylates)
- Nephrotoxic products

Nitrous Oxide

Coadministration of methotrexate with nitrous oxide anesthesia potentiates the effect of methotrexate on folate-dependent metabolic pathways, which may increase the risk of severe methotrexate adverse reactions. Avoid nitrous oxide anesthesia in patients receiving methotrexate. Consider alternative therapies in patients who have received prior nitrous oxide anesthesia.

Folic Acid

Coadministration of methotrexate with folic acid or its derivatives decreases the clinical effectiveness of methotrexate in patients with neoplastic diseases. Methotrexate competes with reduced folates for active transport across cell membranes. Instruct patients to take folic or folinic acid only as directed by their healthcare provider [see Warnings and Precautions (5.10)].

8 USE IN SPECIFIC POPULATIONS

8.1 Pregnancy

Risk Summary

Based on published reports and methotrexate’s mechanism of action, methotrexate can cause embryo-fetal toxicity and fetal death when administered to a pregnant woman [see Clinical Pharmacology (12.1)]. There are no animal data that meet current standards for nonclinical developmental toxicity studies. In pregnant women with non-malignant disease, JYLAMVO is contraindicated. Consider the benefits and risks of JYLAMVO and risks to the fetus when prescribing JYLAMVO to a pregnant patient with a neoplastic disease.

The background risk of major birth defects and miscarriage for the indicated populations are unknown. All pregnancies have a background risk of birth defect, loss, or other adverse outcomes. In the U.S. general population, the estimated background risk of major birth defects and miscarriage in clinically recognized pregnancies is 2% to 4% and 15% to 20%, respectively.

Data

Human Data

Published data from case reports, literature reviews, and observational studies report that methotrexate exposure during pregnancy is associated with an increased risk of embryo-fetal toxicity and fetal death. Methotrexate exposure during the first trimester of pregnancy is associated with an increased incidence of spontaneous abortions and multiple adverse developmental outcomes, including skull anomalies, facial dysmorphism, central nervous system abnormalities, limb abnormalities, and sometimes cardiac anomalies and intellectual impairment. Adverse outcomes associated with exposure during second and third trimesters of pregnancy include intrauterine growth restriction and functional abnormalities. Because methotrexate is widely distributed and persists in the body for a prolonged period, there is a potential risk to the fetus from preconception methotrexate exposure.

A prospective multicenter study evaluated pregnancy outcomes in women taking methotrexate less than or equal to 30 mg/week after conception. The rate of spontaneous abortion and miscarriage in pregnant women exposed to methotrexate was 42% (95% confidence interval [95% CI] 29, 59), which was higher than in unexposed patients with autoimmune disease (22%; 95% CI: 17, 30) and unexposed patients with nonautoimmune disease (17%; 95% CI: 13, 23). Of the live births, the rate of major birth defects in pregnant women exposed to methotrexate after conception was higher than in unexposed patients with autoimmune disease (adjusted odds ratio (OR) 1.8 [95% CI: 0.6, 6]) and unexposed patients with non-autoimmune disease (adjusted OR 3.1 [95% CI: 1, 10]) (2.9%). Major birth defects associated with pregnancies exposed to methotrexate after conception were not always consistent with methotrexate-associated adverse developmental outcomes.

8.2 Lactation

Risk Summary

Limited published literature report the presence of methotrexate in human milk in low amounts, with the highest breast milk to plasma concentration ratio reported to be 0.08:1. There are no data on the effects of methotrexate or its metabolites on the breastfed child or their effects on milk production. Because of the potential for serious adverse reactions in a breastfed child, including myelosuppression, advise women not to breastfeed during treatment with JYLAMVO and for 1 week after the final dose.

8.3 Females and Males of Reproductive Potential

Methotrexate can cause malformations and fetal death at doses less than or equal to the recommended clinical doses [Use in Specific Populations (8.1)].

Pregnancy Testing

Verify the pregnancy status of females of reproductive potential prior to initiating JYLAMVO [see Contraindications (4), Use in Specific Populations (8.1)].

Contraception

Females

JYLAMVO can cause fetal harm when administered to a pregnant woman [see Use in Specific Populations (8.1)]. Advise females of reproductive potential to use effective contraception during treatment with JYLAMVO and for 6 months after the final dose of JYLAMVO.

Males

Methotrexate can cause chromosomal damage to sperm cells. Advise males with female partners of reproductive potential to use effective contraception during treatment with JYLAMVO and for at least 3 months after the final dose of JYLAMVO.

Infertility

Females

Based on published reports of female infertility after treatment with methotrexate, advise females of reproductive potential that methotrexate can cause impairment of fertility and menstrual dysfunction during treatment with JYLAMVO and after the final dose. It is not known if the infertility may be reversed in all affected females.

Males

Based on published reports of male infertility after treatment with methotrexate, advise males of reproductive potential that methotrexate can cause oligospermia or infertility during treatment with JYLAMVO and after the final dose. It is not known if the infertility may be reversed in all affected males.

8.4 Pediatric Use

The safety and effectiveness of JYLAMVO in pediatric patients have been established for the treatment of ALL as part of the combination chemotherapy maintenance regimen and the treatment of pJIA [see Indications and Usage (1), Dosage and Administration (2), and Adverse Reactions (6.1)].

The safety and effectiveness of JYLAMVO have not been established in pediatric patients for the other indications [see Indications and Usage (1)].

8.5 Geriatric Use

Clinical studies of methotrexate did not include sufficient numbers of subjects aged 65 and over to determine whether they respond differently from younger subjects.

8.6 Renal Impairment

Methotrexate elimination is reduced in patients with renal impairment [see Clinical Pharmacology (12.3)]. Patients with renal impairment are at increased risk for methotrexate adverse reactions. Closely monitor patients with renal impairment [creatinine clearance (CLcr) less than 90 mL/min, Cockcroft-Gault] for adverse reactions. Reduce the dosage or discontinue JYLAMVO as appropriate [see Warnings and Precautions (5.8)].

8.7 Hepatic Impairment

The pharmacokinetics and safety of methotrexate in patients with hepatic impairment is unknown. Patients with hepatic impairment may be at increased risk for methotrexate adverse reactions based on the elimination characteristics of methotrexate [see Clinical Pharmacology (12.3)]. Closely monitor patients with hepatic impairment for adverse reactions. Reduce the dosage or discontinue JYLAMVO as appropriate [see Warnings and Precautions (5.5)].

10 OVERDOSAGE

Overdosage, including fatal overdosage, has occurred with methotrexate [see Warnings and Precautions (5.9)].

Manifestations

Manifestations of methotrexate overdosage include adverse reactions reported at pharmacologic doses, particularly hematologic and gastrointestinal reactions (e.g., leukopenia, thrombocytopenia, anemia, pancytopenia, myelosuppression, mucositis, stomatitis, oral ulceration, nausea, vomiting, gastrointestinal ulceration, or gastrointestinal bleeding). In some cases, no symptoms were reported; however, sepsis or septic shock, renal failure, and aplastic anemia were also reported.

Management

Leucovorin and levoleucovorin are indicated for diminishing the methotrexate adverse reactions of methotrexate overdosage. Administer leucovorin or levoleucovorin as soon as possible after methotrexate overdosage. Monitor serum creatinine and methotrexate levels to guide leucovorin or levoleucovorin therapy. Refer to the leucovorin or levoleucovorin prescribing information for additional dosage information.

Glucarpidase is indicated for the treatment of toxic plasma methotrexate concentrations (>1 micromole per liter) in patients with delayed methotrexate clearance due to impaired renal function. Refer to the glucarpidase prescribing information for additional dosage information.

Administer concomitant hydration and urinary alkalinization.

Neither hemodialysis nor peritoneal dialysis has been shown to improve methotrexate elimination; however, methotrexate has been effectively cleared with acute, intermittent hemodialysis using a high-flux dialyzer.

11 DESCRIPTION

Methotrexate is a folate analog metabolic inhibitor with the chemical name of N-[4-[[(2,4 diamino-6-pteridinyl) methyl]methylamino]benzoyl]-L glutamic acid. The molecular formula is C20H22N8O5 and the molecular weight is 454.4 g/mol. The structural formula is:

JYLAMVO (methotrexate) oral solution is a clear yellow solution that contains methotrexate, 2 mg/mL. Inactive ingredients include citric acid, ethylparaben, glycerin, methylparaben sodium, orange flavoring powder, polyethylene glycol, purified water, sodium citrate and sucralose. The target pH of the oral solution is 6.8.

12 CLINICAL PHARMACOLOGY

12.1 Mechanism of Action

Methotrexate inhibits dihydrofolic acid reductase. Dihydrofolates must be reduced to tetrahydrofolates by this enzyme before they can be utilized as carriers of one-carbon groups in the synthesis of purine nucleotides and thymidylate. Therefore, methotrexate interferes with DNA synthesis, repair, and cellular replication. Actively proliferating tissues such as malignant cells, bone marrow, fetal cells, buccal and intestinal mucosa, and cells of the urinary bladder are in general more sensitive to this effect of methotrexate.

The mechanism of action in rheumatoid arthritis and in psoriasis is unknown.

12.3 Pharmacokinetics

Absorption

At doses of 30 mg/m^2 or less, the mean bioavailability is approximately 60%. Peak plasma concentrations are reached within 0.75 to 6 hours following oral administration. Methotrexate may undergo enterohepatic recirculation; however, this pathway has not been fully characterized.

Effect of Food

Food has been shown to delay absorption and reduce peak concentration.

Distribution

Methotrexate in serum is approximately 50% protein bound.

Methotrexate does not penetrate the blood-cerebrospinal fluid barrier at concentrations achieved with the recommended dosages.

Elimination

The elimination half-life of methotrexate is approximately 3 to 10 hours.

Small amounts of methotrexate polyglutamates may remain in tissues for extended periods. The retention and prolonged drug action of these active metabolites vary among different cells, tissues, and tumors.

Nonlinear elimination due to saturation of renal tubular reabsorption has been observed in studies of patients with psoriasis receiving methotrexate doses between 7.5 mg and 30 mg.

Metabolism

Methotrexate is partially metabolized by intestinal flora after oral administration.

Methotrexate primarily undergoes hepatic and intracellular metabolism to active polyglutamated forms which can be converted back to methotrexate by hydrolase enzymes. Methotrexate also undergoes minor metabolism to active 7-hydroxymethotrexate.

Excretion

Methotrexate primarily undergoes renal excretion by glomerular filtration and active tubular secretion that is dependent upon dosage and route of administration.

Biliary excretion accounts for ≤10% of the methotrexate dose.

Specific Populations

The effect of hepatic impairment on the pharmacokinetics of methotrexate is unknown.

Pediatric Patients

In pediatric patients with leukemia, oral absorption (23% to 95%) of methotrexate is variable and dose-dependent. The difference between highest and lowest peak methotrexate concentrations (Cmax 0.11 to 2.3 micromolar after a 20 mg/m^2 dose) was 20-fold. The time to peak concentration (Tmax 0.67 to 4 hours after a 15 mg/m^2 dose) and fraction of dose absorbed is variable. The absorption of doses greater than 40 mg/m^2 is significantly less than that of lower doses.

In pediatric patients with pJIA, plasma concentrations of methotrexate are variable. Following oral administration of methotrexate 6.4 mg/m^2/week to 11.2 mg/m^2/week, mean serum concentrations were 0.59 micromolar (0.03 to 1.40) at 1 hour, 0.44 micromolar (0.01 to 1.00) at 2 hours, and 0.29 micromolar (0.06 to 0.58) at 3 hours.

In pediatric patients receiving methotrexate for acute lymphoblastic leukemia (6.3 mg/m^2 to 30 mg/m^2) or for JIA (3.75 mg/m^2 to 26.2 mg/m^2), the terminal half-life has been reported to range from 0.7 to 5.8 hours or from 0.9 to 2.3 hours, respectively.

Patients with Renal Impairment

The elimination half-life of methotrexate is variable and increases with the severity of renal impairment.

13 NONCLINICAL TOXICOLOGY

13.1 Carcinogenesis, Mutagenesis, Impairment of Fertility

Methotrexate has been evaluated in a number of animal studies for carcinogenic potential with inconclusive results. Although there is evidence that methotrexate causes chromosomal damage to animal somatic cells and human bone marrow cells, the clinical significance remains uncertain.

15 REFERENCES

1. “OSHA Hazardous Drugs.” OSHA. http://www.osha.gov/SLTC/hazardousdrugs/index.html.

16 HOW SUPPLIED / STORAGE AND HANDLING

JYLAMVO is supplied as a clear yellow oral solution that contains 2 mg of methotrexate per mL. It is packaged in an amber type III glass bottle with tamper evident child-resistant closure (polypropylene with expanded polyethylene liner) containing 60 mL of oral solution.

Each pack contains one bottle, a low-density polyethylene (LDPE) bottle adaptor and a 10 mL white polypropylene dosing syringe (with major graduations at every 1 mL and minor graduations at every 0.25 mL) (NDC 81927-204-01).

Store JYLAMVO at 20°C to 25°C (68°F to 77°F) excursions permitted to 15°C to 30°C (59°F to 86°F) [see USP Controlled Room Temperature].

In Use storage conditions: Store JYLAMVO at room temperature 20°C to 25°C (68°F to 77°F). Keep the bottle tightly closed. After first opening, discard any unused medicine after 3 months.

JYLAMVO is a hazardous drug. Follow applicable special handling and disposal procedures.^1

17 PATIENT COUNSELING INFORMATION

Advise the patient to read the FDA-approved patient labeling (Patient Information).

Embryo-Fetal Toxicity

- Advise females of reproductive potential of the potential risk to a fetus and to inform their healthcare provider of a known or suspected pregnancy [see Contraindications (4), Warnings and Precautions (5.1), Use in Specific Populations (8.1)].
- Advise females of reproductive potential to use effective contraception during treatment with JYLAMVO and for 6 months after the final dose [see Use in Specific Populations (8.3)].
- Advise males of reproductive potential to use effective contraception during treatment with JYLAMVO and for at least 3 months after the final dose [see Use in Specific Populations (8.3)].

Hypersensitivity Reactions

Advise patients and their caregivers of the potential risk of hypersensitivity and that JYLAMVO is contraindicated in patients with a history of hypersensitivity reactions to methotrexate. Instruct patients to seek immediate medical attention for signs of a hypersensitivity reaction [see Warnings and Precautions (5.2)].

Myelosuppression and Serious Infections

Inform patients and their caregivers that JYLAMVO can cause myelosuppression and the need for frequent monitoring of blood cell counts. Advise patients and their caregivers to immediately report new onset fever, symptoms of infection, easy bruising or persistent bleeding to their healthcare provider [see Warnings and Precautions (5.3, 5.11)].

Gastrointestinal Toxicity

Advise patients and their caregivers to report new or worsening diarrhea, vomiting, or stomatitis to their healthcare provider. Advise patients to immediately contact their healthcare provider for high fever, rigors, persistent or severe abdominal pain, severe constipation, hematemesis, or melena [see Warnings and Precautions (5.4)].

Hepatotoxicity

Advise patients and their caregivers to report signs or symptoms of hepatic toxicity to their healthcare provider [see Warnings and Precautions (5.5)].

Pulmonary Toxicity

Advise patients and their caregivers to report new or worsening cough, fever, or dyspnea to their healthcare provider [see Warnings and Precautions (5.6)].

Dermatologic Reactions

Advise patients and their caregivers that JYLAMVO can cause serious skin rash and to immediately contact their healthcare provider for new or worsening skin rash. Advise patients and their caregivers to avoid excessive sun exposure and use sun protection measures [see Warnings and Precautions (5.7)].

Renal Toxicity

Advise patients and their caregivers to immediately contact their healthcare provider for signs or symptoms of renal toxicity, such as marked increases or decreases in urinary output [see Warnings and Precautions (5.8)].

Risk of Serious Adverse Reactions with Medication Error

For patients who are prescribed a once weekly dosing regimen, advise patients and caregivers that the recommended dosage is to be taken once weekly as a single dose and that mistakenly taking the recommended weekly dosage once daily has led to fatal adverse reactions [see Warnings and Precautions (5.9)].

Importance of Proper Dosage and Administration

Before use, instruct patients and caregivers on how to measure and administer the recommended dosage, utilizing the copackaged syringe and bottle adaptor and that a teaspoon is not an appropriate measuring device. Advise patients and caregivers to only use the copackaged syringe and that a household spoon is not an accurate measuring device [see Dosage and Administration (2)].

Neurotoxicity

Advise patients and their caregivers to report new neurological signs or symptoms to their healthcare provider [see Warnings and Precautions (5.12)].

Secondary Malignancies

Advise patients on the risk of second primary malignancies during treatment with JYLAMVO [see Warnings and Precautions (5.13)].

Ineffective Immunization and Risks Associated with Live Vaccines

Advise patients to avoid receiving vaccines during treatment with JYLAMVO because they may not be effective and live virus vaccines may cause infections [see Warnings and Precautions (5.15)].

Lactation

Instruct women not to breastfeed during treatment with JYLAMVO and for 1 week after the final dose [see Use in Specific Populations (8.2)].

Infertility

Advise females and males of reproductive potential that methotrexate may impair fertility [see Warnings and Precautions (5.16), Use in Specific Populations (8.3)].

Drug Interactions

Advise patients and caregivers to inform their healthcare provider of all concomitant medications, including prescription medicines, over-the-counter drugs, vitamins, and herbal products [see Drug Interactions (7)].

Proper Storage and Disposal

Advise patients to store JYLAMVO at room temperature (20°C to 25°C/ 68°F to 77°F). Once the bottle has been opened, any remaining medication must be disposed of after 90 days. Inform patients and caregivers of the need for proper disposal of the medication, bottle, and syringe [see References (15)]. This medicine should not be disposed of in wastewater or household waste.

Manufactured By:

SGS Quay Pharmaceuticals Ltd., Deeside, UK

Distributed By:

Shorla Oncology Inc., Cambridge, MA 02142, USA.

Version: JYLPI010

Patient Information
JYLAMVO® (Jye lam voe)
(methotrexate)

oral solution

What is the most important information I should know about JYLAMVO®?

JYLAMVO can cause serious side effects that may be severe and lead to death, including:

Harm to an unborn baby, including birth defects or death of an unborn baby.

Females who can become pregnant:

- Your healthcare provider should do a pregnancy test before you start taking JYLAMVO to see if you are pregnant.
  - If you are being treated for a medical condition other than cancer, do not take JYLAMVO if you are pregnant. See “Who should not take JYLAMVO?”
  - If you are taking JYLAMVO to treat your cancer, you and your healthcare provider will decide if you will take JYLAMVO if you are pregnant.
  - Use effective birth control (contraception) during treatment and for 6 months after your final dose of JYLAMVO. Ask your healthcare provider what forms of birth control you can use during this time.
  - Tell your healthcare provider right away if you become pregnant or think you are pregnant during treatment with JYLAMVO.

Males with female partners who are able to become pregnant:

- Use effective birth control during treatment and for at least 3 months after your final dose of JYLAMVO.
- Tell your healthcare provider right away if your female partner becomes pregnant during treatment with JYLAMVO.

Severe allergic reactions. Severe allergic reactions can happen with JYLAMVO. Signs and symptoms of a severe allergic reaction may include:

- skin rash, itching and hives
- swelling of the face, lips, tongue, or throat
- dizziness
- trouble breathing
- wheezing

- fast heart rate
- feeling faint
- stomach-area pain
- vomiting or diarrhea

Do not take JYLAMVO if you have had a severe allergic reaction to methotrexate in the past.

Get medical help right away if you develop any of the signs or symptoms of a severe allergic reaction listed above.

Decreased blood cell counts. JYLAMVO can affect your bone marrow and cause decreases in red blood counts, white blood cell counts, and platelets that can be severe and life-threatening.

- Your healthcare provider will check your blood cell counts when you start and during treatment with JYLAMVO.

Call your healthcare provider right away if you develop any of the following:

- a new fever
- symptoms of infection
- easy bruising or bleeding that will not stop (persistent bleeding)

Severe stomach and intestine problems (gastrointestinal) problems.

- Diarrhea, vomiting, nausea, and mouth sores can happen in people who take JYLAMVO.
- Inflammation of the intestine with severe bleeding and a tear in the intestinal wall (perforation) have happened with methotrexate and cause death.
- People who have stomach ulcers (peptic ulcer disease) or ulcerative colitis (UC) have a greater risk of developing severe stomach or intestine problems with JYLAMVO.

Tell your healthcare provider if you develop new or worsening diarrhea, vomiting, or mouth sores during treatment with JYLAMVO.

Tell your healthcare provider right away if you develop high fever, shaking chills (rigors), pain in your stomach-area (abdomen) that will not go away or is severe, severe constipation, if you are vomiting blood or have blood in your stools.

Liver problems. JYLAMVO can cause severe liver problems including liver scarring (fibrosis), cirrhosis, and liver failure that may not get better (possibly irreversible) and can cause death.

- In people with psoriasis who take JYLAMVO, liver fibrosis or cirrhosis may happen without any symptoms or abnormal liver tests. The risk for liver problems in people with psoriasis increases with the amount of JYLAMVO taken over time.
- Your healthcare provider will do tests to monitor your liver function before you start and during treatment with JYLAMVO.

Tell your healthcare provider if you have any signs or symptoms of liver problems during treatment with JYLAMVO, including:

- tiredness
- easy bleeding or bruising
- loss of appetite
- nausea
- difficulty thinking clearly

- swelling in your legs, feet or ankles
- weight loss
- itchy skin
- yellowing of your skin or the white part of your eyes
- weakness

Lung problems. Lung problems can happen suddenly (acute) with JYLAMVO or they can develop over a long period-of-time (chronic). Lung problems may not get better (possibly irreversible) and can cause death. Tell your healthcare provider if you have any new or worsening symptoms including: cough (especially a dry cough), fever, or trouble breathing.

Severe skin reactions. Severe skin reactions can happen with JYLAMVO and can lead to death.

- In people with psoriasis: Your psoriasis may get worse if you are exposed to sunlight or other types of ultraviolet light.
- JYLAMVO can cause reactivation of skin reactions that can happen after radiation therapy (radiation recall dermatitis) and cause sunburn to come back (photodermatitis).

Limit sunlight exposure during treatment with JYLAMVO. Use sunscreen and wear protective clothing when you will be exposed to sunlight during treatment with JYLAMVO.

Tell your healthcare provider right away about any new or worsening skin rash during treatment with JYLAMVO.

Kidney problems. Kidney problems can happen with JYLAMVO, including kidney failure which can happen suddenly (acute) and may not go away (irreversible).

Your healthcare provider will check your kidney function before you start and during treatment with JYLAMVO.

Tell your healthcare provider right away if you have any signs or symptoms of kidney problems, including:

- a big change (either increase or decrease)
  in the amount of urine you produce
- swelling in your legs, ankles or feet

- shortness of breath
- tiredness
- weight gain

See “What are the possible side effects of JYLAMVO” for more information about side effects.

What is JYLAMVO?

JYLAMVO is a prescription medicine used:

- in combination with other chemotherapy medicines in adults and children, for maintenance treatment of acute lymphoblastic leukemia (ALL)
- to treat adults with mycosis fungoides (cutaneous T-cell lymphoma)
- in combination with other therapies to treat adults with non-Hodgkin lymphoma that has come back (relapsed) or did not respond to previous treatment (refractory)
- to treat adults with rheumatoid arthritis
- to treat children with polyarticular juvenile idiopathic arthritis (pJIA)
- to treat adults with severe psoriasis

It is not known if JYLAMVO is safe and effective in children for the treatment of any medical condition other than ALL as part of a combination regimen used for maintenance therapy of their cancer, and pJIA.

It is not known if JYLAMVO is safe in people with liver problems.

Do not take JYLAMVO if you:

- are pregnant and are being treated or will be treated with JYLAMVO for rheumatoid arthritis, pJIA, severe psoriasis or for any medical condition other than cancer. JYLAMVO can cause harm to an unborn baby, including birth defects or death of an unborn baby. See “What is the most important information I should know about JYLAMVO?”
- have or had a severe allergic reaction to JYLAMVO or any other medicine containing methotrexate. See “What is the most important information I should know about JYLAMVO?” See the end of this Patient Information leaflet for a complete list of ingredients in JYLAMVO.

Before taking JYLAMVO tell your healthcare provider about all of your medical conditions, including if you:

- have kidney problems or are receiving dialysis treatments.
- have liver problems.
- drink alcohol-containing beverages and, during treatment with JYLAMVO, if there are any changes in the amount of alcoholic beverages you drink.
- have fluid in your stomach-area (ascites).
- have lung problems or fluid in your lungs (pleural effusion).
- plan to have any surgeries with general anesthesia, including dental surgery.
- have stomach ulcers (peptic ulcer disease).
- have ulcerative colitis.
- have recently received or are scheduled to receive a vaccine. You should not receive live vaccines during treatment with JYLAMVO. These vaccines may not be safe or may not work as well during treatment with JYLAMVO.
- are breastfeeding or plan to breastfeed. JYLAMVO may pass into your breast milk. Do not breastfeed during treatment and for 1 week after your last dose of JYLAMVO.

Tell your healthcare provider about all the medicines you take, including prescription and over-the-counter medicines, vitamins and herbal supplements. JYLAMVO and certain other medicines can affect each other and cause serious side effects. Do not start or change any medicines unless you have talked to your healthcare provider and your healthcare provider has told you it is safe. Know all the medicines that you take and keep a list of them with you at all times to show healthcare providers and pharmacists.

How should I take JYLAMVO?

- JYLAMVO is for use by mouth only (oral use).
- Take JYLAMVO exactly as prescribed by your healthcare provider. Your dose of JYLAMVO and when you take it will depend on the condition that is being treated.
- Do not take more JYLAMVO than prescribed. Do not change your dose of JYLAMVO unless your healthcare provider tells you to.
- Taking more JYLAMVO than prescribed or taking JYLAMVO more often than prescribed, can lead to severe side effects and cause death.
- If you take too much JYLAMVO call your healthcare provider or go to your nearest hospital emergency room right away. You will need to receive a medicine as soon as possible to help reduce side effects that could be severe and could cause death.
- If you miss taking a dose of JYLAMVO, call your healthcare provider for instructions about when to take your next dose of JYLAMVO.

If you are taking JYLAMVO for treatment of severe psoriasis, rheumatoid arthritis or polyarticular juvenile idiopathic arthritis:

- Take your JYLAMVO dose 1 time each week, not every day. Severe side effects and death have happened in people who mistakenly have taken JYLAMVO every day instead of 1 time each week.
- Take a folic acid or folinic acid supplement every day during treatment with JYLAMVO, as instructed by your healthcare provider, to help reduce the chance of developing certain side effects, such as mouth sores.

If you are taking JYLAMVO to treat your cancer:

- Follow your healthcare provider’s instructions about how much JYLAMVO to take and when to take it.
- Do not take folic acid or folinic acid during treatment with JYLAMVO unless your healthcare provider tells you to. Taking folic acid or folinic acid with JYLAMVO may make your JYLAMVO treatment less effective.

Instructions for Using JYLAMVO

Each pack of JYLAMVO contains a bottle of medicine with a cap, a bottle neck adaptor, and a white dosing syringe. Always use the dosing syringe provided in the pack to take JYLAMVO. A household teaspoon is not an accurate measuring device.

Note: the dosing syringe measures the amount of oral solution in mL and JYLAMVO contains 2 mg of methotrexate in 1 mL of solution.

Read and carefully follow the instructions below:

1. Put on disposable gloves before handling JYLAMVO.
2. Shake the bottle.
3. Remove the bottle cap and push the adaptor firmly into the top of the bottle.
4. Push the tip of the dosing syringe into the hole in the adaptor.
5. Turn the bottle upside down.
6. Pull the syringe plunger back slowly so that the medicine is drawn from the bottle into the syringe until the widest part of the white syringe plunger is lined up to the black syringe marking of the prescribed dose. Do not measure to the narrow tip of the plunger. If there are air bubbles in the syringe, use the syringe plunger to push the medicine back into the bottle then draw the medicine into the syringe again until there are no more air bubbles.
7. Turn the bottle back upright and carefully remove the syringe from the adaptor, holding the syringe by the barrel rather than the plunger.
8. Check that the dose in the syringe is correct.
9. Make sure that you are sitting up or standing before taking the medicine.
10. Gently place the tip of the syringe in your mouth and direct it to the inside of your cheek.
11. Slowly and gently push the plunger down to gently squirt the medicine into the inside of your cheek. Do not pushdown on the plunger too hard or squirt the medicine to the back of the mouth or throat as this may cause choking. The plunger should be pushed down gently and completely until it clicks into place.
12. Remove the syringe from your mouth.
13. Swallow the medicine and then drink some water, making sure no medicine is left in the mouth.
14. Put the cap back on the bottle with the adaptor left in place. Make sure that the cap is tightly closed.
15. Wash the syringe immediately after use with warm, soapy water and rinse well. The syringe should be held underwater and the plunger drawn in and out several times until all of the medicine is removed from inside the syringe including the tip. Remove the plunger from the syringe barrel and wash both parts well in the warm, soapy water. Each part should then be rinsed well under cold water and any extra water shaken off before wiping dry with a clean paper towel. The plunger and barrel should be stored in a clean dry container with the medicine. All parts of the syringe should be completely dry before putting the plunger back into the syringe and using it for the next dose.

What are the possible side effects of JYLAMVO?

JYLAMVO can cause serious side effects that may be severe and lead to death including:

- See “What is the most important information I should know about JYLAMVO?”
- Serious infections. People who take methotrexate have an increased risk of developing infections that can be life-threatening or cause death. These infections may include: bacterial, fungal, or viral infections, including Pneumocystis jiroveci pneumonia, invasive fungal infections, hepatitis B infection that comes back (reactivation), tuberculosis infection that may be new or reactivation, and Herpes zoster or cytomegalovirus (CMV) that spreads throughout the body (disseminated).
- Tell your healthcare provider right away if you develop a new fever or if you have any symptoms of infection during treatment with JYLAMVO.
- Brain and spinal cord (nervous system) problems. Methotrexate can cause nervous system problems that can be severe and last for a short time or last for a long time. These nervous system problems can get progressively worse, may not get better (irreversible), and can cause death. The risk for a certain nervous system problem called leukoencephalopathy is increased in people who have had radiation treatment to their head (cranial radiation) in the past.
  Tell your healthcare provider about any new nervous system symptoms that you develop during treatment with JYLAMVO.
- New (secondary) cancers. New (secondary) cancers can happen in people who take JYLAMVO.
  - In people with psoriasis, the risk of new skin cancers is increased with JYLAMVO and further increased if you take the medicine cyclosporine after receiving treatment with JYLAMVO.
  - Certain blood cancers can happen during treatment with JYLAMVO. In some cases, these blood cancers may completely go away (regress completely) after JYLAMVO is stopped.
- Tumor lysis syndrome (TLS). TLS is caused by the fast breakdown of cancer cells. TLS can cause kidney failure and the need for dialysis treatment, abnormal heart rhythm, seizure, and sometimes death. Your healthcare provider may do blood tests to check you for TLS if you are receiving JYLAMVO as a cancer treatment.
- Possible fertility problems (infertility) in males and females. JYLAMVO can cause fertility problems in males and females, and can cause sperm production to stop in males, and menstrual problems in females. Males may not be able to father a child. Females may not be able to become pregnant. It is not known if your fertility may return. Talk with your healthcare provider about your risk for infertility if this is a concern for you.

The most common side effects of JYLAMVO include:

- mouth sores
- low white blood cells. See“What is the most important information I should know about JYLAMVO?”
- nausea, upset stomach

These are not all the possible side effects of JYLAMVO. Ask your healthcare provider or pharmacist for more information. Call your doctor for medical advice about side effects. You may report side effects to FDA at 1-800- FDA-1088.

How should I store JYLAMVO?

- Store the JYLAMVO bottle at room temperature between 68°F to 77°F (20°C to 25°C).
- Keep JYLAMVO tightly closed with the cap on the bottle.
- Store the dosing syringe in a clean, dry place when not in use.
- Use JYLAMVO within 3 months of first opening the bottle. After 3 months throw away (dispose of) any remaining medicine. Ask the pharmacist how to throw away (dispose of) unused medicine, the bottle and the dosing syringe. This medicine should not be disposed of in wastewater or household waste.

Keep JYLAMVO and all medicines out of the reach of children.

General information about the safe and effective use of JYLAMVO.

Medicines are sometimes prescribed for purposes other than those listed in a Patient Information leaflet. Do not use JYLAMVO for a condition for which it was not prescribed. Do not give JYLAMVO to other people, even if they have the same symptoms that you have. It may harm them. This Patient Information leaflet summarizes the most important information about JYLAMVO. If you would like more information, talk with your healthcare provider. You can ask your pharmacist or healthcare provider for information about JYLAMVO that is written for health professionals.

What are the ingredients in JYLAMVO?

Active Ingredient: methotrexate

Inactive Ingredients: citric acid, ethylparaben, glycerin, methylparaben sodium, orange flavoring powder, polyethylene glycol, purified water, sodium citrate and sucralose.

Manufactured By:
SGS Quay Pharmaceuticals Ltd., Deeside, UK

Distributed By:
Shorla Oncology Inc., Cambridge, MA 02142, USA Version: JYLPL007

This Patient Information has been approved by the U.S. Food and Drug Administration Revised: 10/2025

PRINCIPAL DISPLAY PANEL

WARNING: Hazardous drug

NDC 81927-204-01

Jylamvo®

(methotrexate)

Oral Solution

2 mg/mL

For Oral Use Only

Attention Pharmacist:
Dispense the accompanying Patient
Information to each patient.

60 mL

Rx Only

WARNING: hazardous drug

NDC 81927-204-01

Jylamvo®

(methotrexate)

Oral Solution

2 mg/mL

For Oral Use Only

Attention Pharmacist:
Dispense the accompanying Patient
Information to each patient.

60 mL

Rx Only